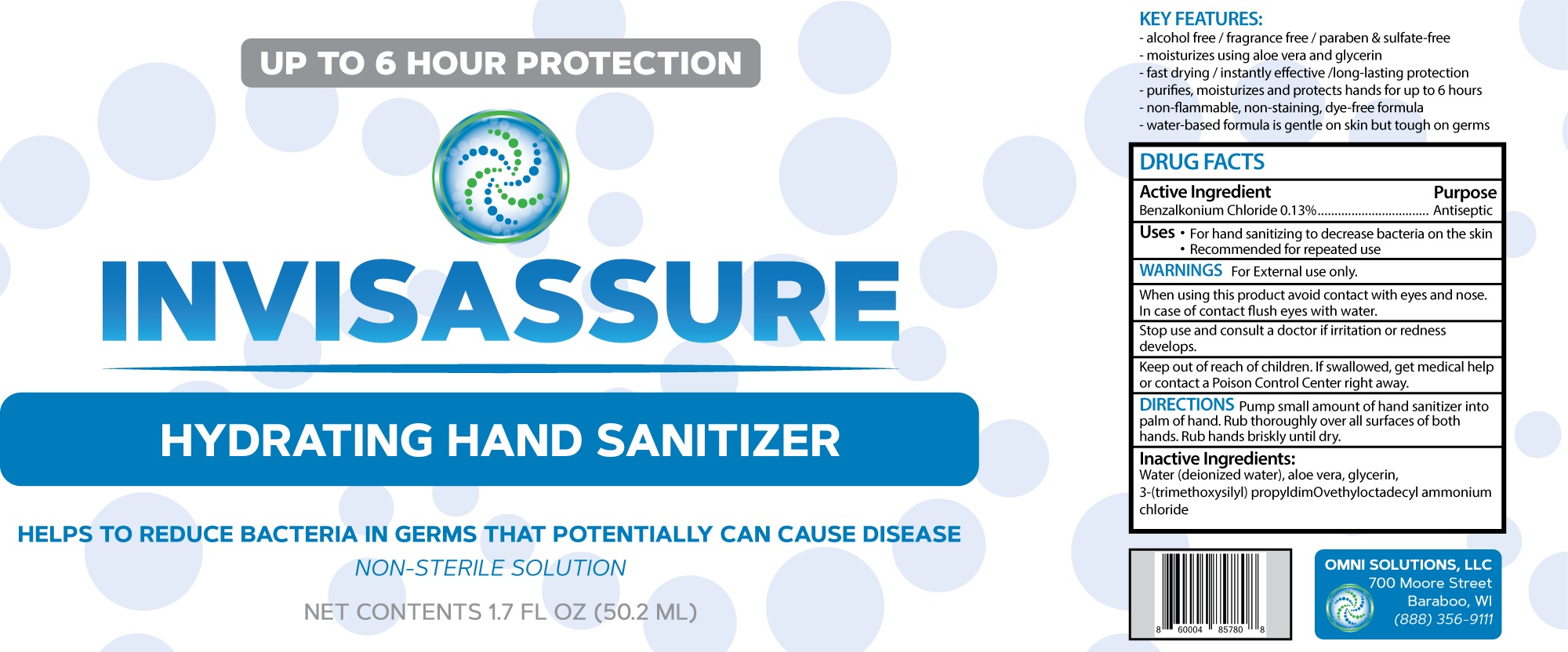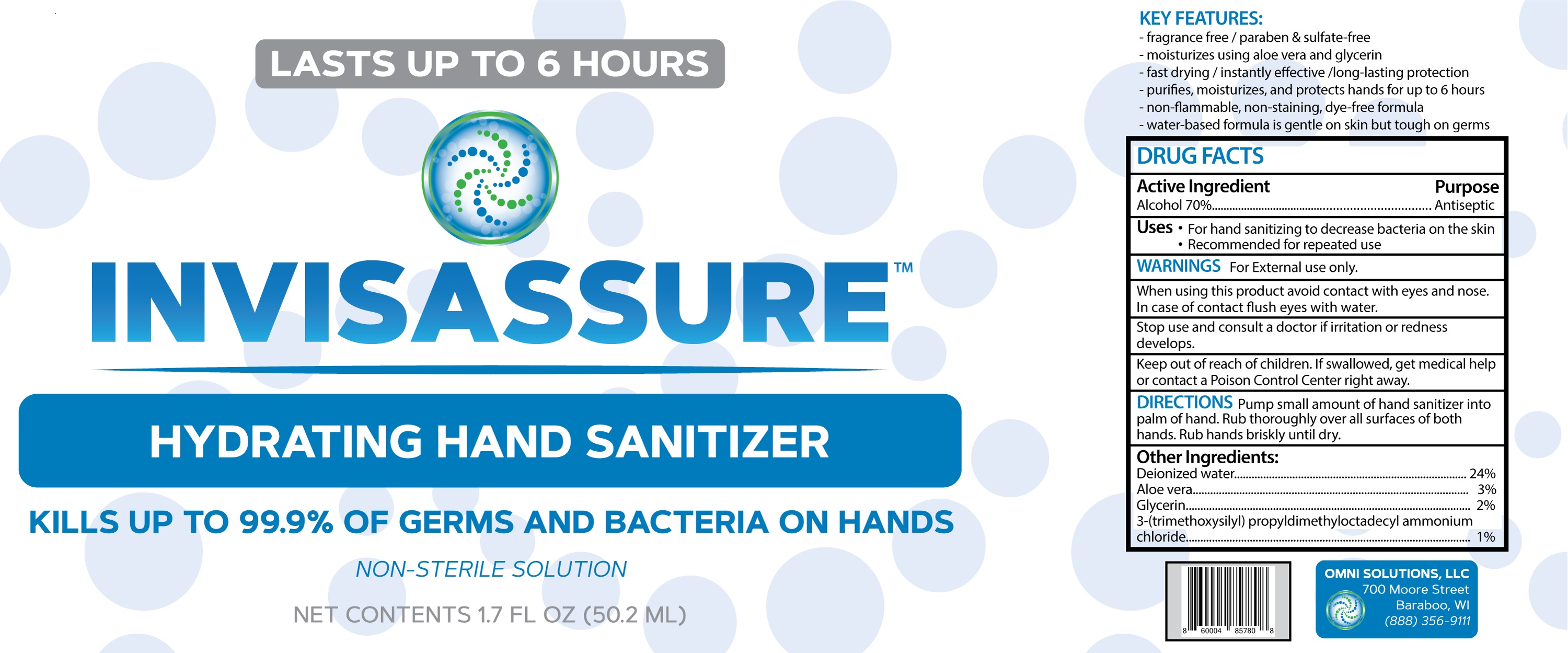 DRUG LABEL: InvisAssure Hydrating  Hand Sanitizer
NDC: 75153-013 | Form: LIQUID
Manufacturer: Hangzhou Changing Time Biotechnology Co.,Ltd
Category: otc | Type: HUMAN OTC DRUG LABEL
Date: 20210311

ACTIVE INGREDIENTS: BENZALKONIUM CHLORIDE 0.13 g/100 mL
INACTIVE INGREDIENTS: WATER; ALOE VERA LEAF; GLYCERIN; DIMETHYLOCTADECYL(3-(TRIMETHOXYSILYL)PROPYL)AMMONIUM CHLORIDE

75153-013
InvisAssure Hydrating Hand Sanitizer

ACTIVE INGREDIENT

Benzalkonium Chloride（0.13%）

PURPOSE

Antiseptic

USES

For hand sanitizing to decrease bacteria on the skin
Recommended for repeated use

WARNINGS

For External use only.

When using this product avoid contact with eyes and nose.
In case of contact flush eyes witth water.

Stop use and consult a docttor if irritation or redness dlevelops.

Keep out of reach of child reni. If swallowed, get medical help or contact a Poison Control Center right away.

DO NOT USE

/

WHEN USING SECTION

When using this product avoid contact with eyes and nose.
In case of contact flush eyes witth water.

Stop use and consult a docttor if irritation or redness dlevelops.

KEEP OUT OF REACH OF CHILDREN

Keep out of reach of child reni. If swallowed, get medical help or contact a Poison Control Center right away.

DIRECTIONS

Pump small amount of hand sanitizer into palm of harnd. Rub thoroughly over all surfaces of both hands. Rub hands briskly until dry.

INACTIVE INGREDIENTS

Water (deionized watter), aloe vera, glycerin, 3-(trimethoxys.itiyl) PropyldimOvethyloctadecyl ammonium chloride

Package Label - Principal Display Panel

75153-013-01 50.2mL

75153-013-02 50.2mL